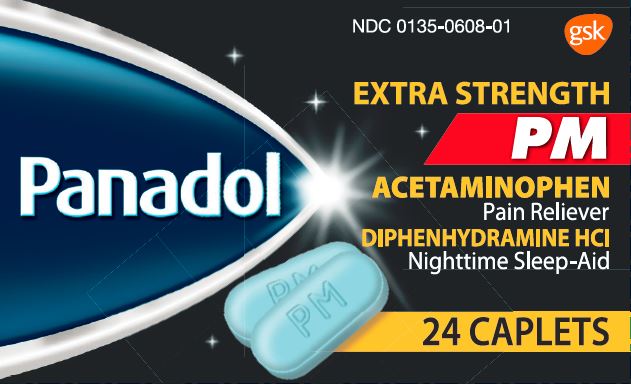 DRUG LABEL: PANADOL

NDC: 0135-0608 | Form: TABLET, FILM COATED
Manufacturer: Haleon US Holdings LLC
Category: otc | Type: HUMAN OTC DRUG LABEL
Date: 20240206

ACTIVE INGREDIENTS: ACETAMINOPHEN 500 mg/1 1; DIPHENHYDRAMINE HYDROCHLORIDE 25 mg/1 1
INACTIVE INGREDIENTS: CARNAUBA WAX; CROSPOVIDONE (120 .MU.M); FD&C BLUE NO. 1; FD&C BLUE NO. 2; HYPROMELLOSE, UNSPECIFIED; MAGNESIUM STEARATE; MICROCRYSTALLINE CELLULOSE; POLYETHYLENE GLYCOL, UNSPECIFIED; POLYSORBATE 80; POVIDONE, UNSPECIFIED; STARCH, CORN; SODIUM STARCH GLYCOLATE TYPE A POTATO; STEARIC ACID; TITANIUM DIOXIDE

Drug Facts

Active ingredients (in each caplet)

Acetaminophen 500 mg

Diphenhydramine HCl 25 mg

Purposes

Pain reliever

Nighttime sleep-aid

Uses

- temporary relief of occasional headaches and minor aches and pains with accompanying sleeplessness

Warnings

Liver warning:This product contains acetaminophen. Severe liver damage may occur if you take

- more than 4,000 mg of acetaminophen in 24 hours
- with other drugs containing acetaminophen
- 3 or more alcoholic drinks every day while using this product

Allergy alert:

acetaminophen may cause severe skin reactions. Symptoms may include:

- skin reddening
- blisters
- rash

If a skin reaction occurs, stop use and seek medical help right away.

Do not use

- with any other drug containing acetaminophen (prescription or nonprescription). If you are not sure whether a drug contains acetaminophen, ask a doctor or pharmacist.
- with any other product containing diphenhydramine, even one used on skin
- in children under 12 years of age
- if you are allergic to acetaminophen or any of the inactive ingredients in this product

Ask a doctor before use if you have

- liver disease
- glaucoma
- a breathing problem such as emphysema or chronic bronchitis
- trouble urinating due to an enlarged prostate gland

Ask a doctor or pharmacist before use if you are taking

- the blood thinning drug warfarin
- sedatives or tranquilizers

When using this product

- drowsiness will occur
- avoid alcoholic drinks
- be careful when driving a motor vehicle or operating machinery

Stop use and ask a doctor if

- sleeplessness persists continuously for more than 2 weeks. Insomnia may be a symptom of a serious underlying medical illness.
- pain gets worse or lasts more than 10 days
- redness or swelling is present
- any new symptoms appear

These could be signs of a serious condition.

If pregnant or breast-feeding,

ask a health professional before use.

Overdose warning:

Taking more than the recommended dose can cause serious health problems. In case of overdose, get medical help or contact a Poison Control Center right away. Quick medical attention is critical for adults as well as for children even if you do not notice any signs or symptoms.

Directions

- do not take more than directed(see overdose warning)
- adults and children 12 years of age and over: take 2 caplets at bedtime, if needed, or as directed by a doctor
- do not give to children under 12 years of age

Other information

- store below 25°C (77°F)

Inactive ingredients

carnauba wax, crospovidone, FD&C blue #1 aluminum lake, FD&C blue #2 aluminum lake, hypromellose, magnesium stearate, microcrystalline cellulose, polyethylene glycol, polysorbate 80, povidone, pregelatinized starch, sodium starch glycolate, stearic acid, titanium dioxide

Questions or comments?

1-800-455-7139

Principal Display Panel

NDC 0135-0608-01

PANADOL

EXTRA STRENGTH

PM

ACETAMNOPHEN

Pain Reliever

DIPHENHYDRAMINE HCl

Nighttime Sleep-Aid

24 CAPLETS

Tamper-Evident Feature:Do not use if printed bottle seal (under cap) is missing or broken.

READ AND KEEP CARTON FOR COMPLETE INFORMATION

Trademarks are owned by or licensed to the GSK group of companies.

Distributed by:

GSKConsumer Healthcare, Warren, NJ 07059

©2016 GSK group of companies or its licensor.

101639XE